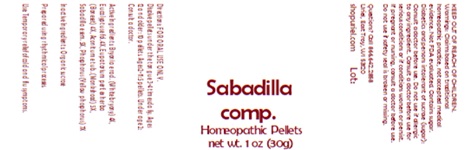 DRUG LABEL: Sabadilla comp.
NDC: 48951-8429 | Form: PELLET
Manufacturer: Uriel Pharmacy, Inc
Category: homeopathic | Type: HUMAN OTC DRUG LABEL
Date: 20241213

ACTIVE INGREDIENTS: BRYONIA ALBA ROOT 4 [hp_X]/1 1; EUCALYPTUS GUM 4 [hp_X]/1 1; ACONITUM NAPELLUS 5 [hp_X]/1 1; EUPATORIUM PERFOLIATUM FLOWERING TOP 4 [hp_X]/1 1; SCHOENOCAULON OFFICINALE SEED 5 [hp_X]/1 1; PHOSPHORUS 7 [hp_X]/1 1
INACTIVE INGREDIENTS: SUCROSE

Sabadilla comp.

INDICATIONS AND USAGE

Directions: FOR ORAL USE ONLY.

DOSAGE AND ADMINISTRATION

Dissolve pellets under the tongue 3-4 times daily. Ages 12 and older: 10 pellets. Ages 2-11: 5 pellets. Under age 2: Consult a doctor.

ACTIVE INGREDIENT

Active Ingredients: Bryonia e rad. (White bryony) 4X, Eucalyptus e fol. 4X, Eupatorium perf. ex herba (Boneset) 4X, Aconitum e tub. (Monkshood) 5X, Sabadilla e sem. 5X, Phosphorus (Yellow phosphorus) 7X

Inactive Ingredients: Organic sucrose

Prepared using rhythmical processes.

PURPOSE

Use: Temporary relief of cold and flu symptoms.

KEEP OUT OF REACH OF CHILDREN.

WARNINGS

Warnings: Claims based on traditional homeopathic practice, not accepted medical evidence. Not FDA evaluated. Contains sugar. Diabetics and persons intolerant of sucrose (sugar): Consult a doctor before use. Do not use if allergic to any ingredient. Consult a doctor before use for serious conditions or if conditions worsen or persist. If pregnant or nursing, consult a doctor before use. Do not use if safety seal is broken or missing.

Questions? Call 866.642.2858
Uriel, East Troy, WI 53120
shopuriel.com Lot: